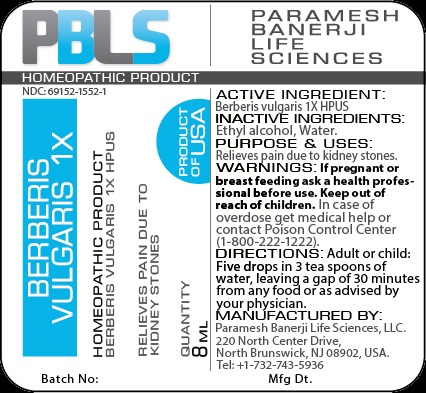 DRUG LABEL: Berberis vulgaris 1X
NDC: 69152-1552 | Form: LIQUID
Manufacturer: Paramesh Banerji Life Sciences LLC
Category: homeopathic | Type: HUMAN PRESCRIPTION DRUG LABEL
Date: 20150825

ACTIVE INGREDIENTS: BERBERIS VULGARIS ROOT BARK 1 [hp_X]/8 mL
INACTIVE INGREDIENTS: ALCOHOL; WATER

Active Ingredient

Berberis vulgaris 1X HPUS

Inactive Ingredients

Ethyl alcohol, Water

Purpose

Relieves pain due to kidney stones

Uses

Relieves pain due to kidney stones

Warnings

If pregnant or breast feeding ask a health professional before use.

Keep out of reach of children. In case of overdose, get medical help or contact a Poison Control Center (1-800-222-1222) right away.

Direction

Adult or child: Five drops in 3 tea spoons of water, leaving a gap of 30 minutes from any food or as advised by your physician.

Manufactured by

Paramesh Banerji Life Sciences, LLC

220 North Center Drive

North Brunswick, NJ 08902, USA

Tel: +1-732-743-5936

Principal Display Panel

Homeopathic Product

NDC: 69152-1552-1

Berberis vulgaris 1X

Homeopathic Product

Berberis vulgaris 1X HPUS

Relieves pain due to kidney stones

Quantity

8 mL

Product of USA